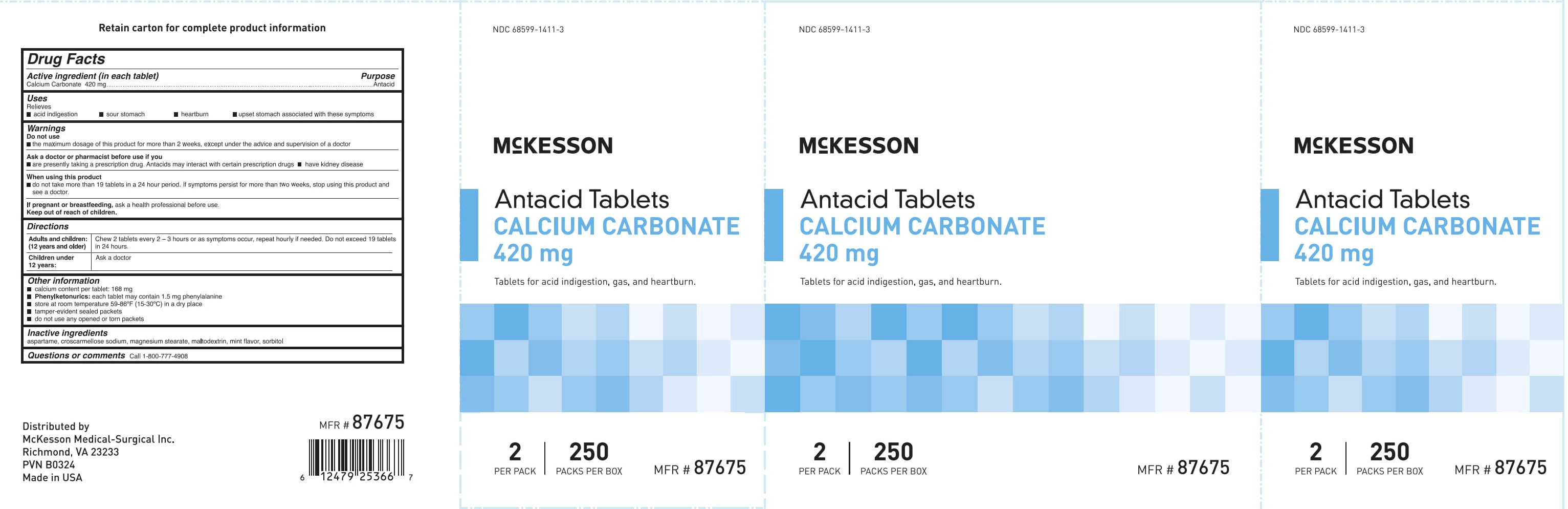 DRUG LABEL: McKesson Antacid Calcium  Carbonate
NDC: 68599-1411 | Form: TABLET, CHEWABLE
Manufacturer: McKesson Medical-Surgical
Category: otc | Type: HUMAN OTC DRUG LABEL
Date: 20250908

ACTIVE INGREDIENTS: CALCIUM CARBONATE 420 mg/1 1
INACTIVE INGREDIENTS: ASPARTAME; SORBITOL; MAGNESIUM STEARATE; CROSCARMELLOSE SODIUM; MALTODEXTRIN

McKesson Antacid Tablets Calcium Carbonate 420 mg

Drug Facts

Active ingredient (in each tablet)

Calcium Carbonate 420 mg

Purpose

Antacid

Uses

Relieves

- acid indigestion
- sour stomach
- heartburn
- upset stomach associated with these symptoms

Warnings

Do not use

- the maximum dosage of this product for more than 2 weeks except under the advice and supervision of a doctor

Ask a doctor or pharmacist before use if you are

- presently taking a prescription drug. Antacids may interact with certain prescription drugs.
- have kidney disease

When using this product

- do not take more than 19 tablets in a 24 hour period. If symptoms persist for more than 2 weeks, stop using this product and see a doctor.

PREGNANCY OR BREAST FEEDING

If pregnant or breast feeding, ask a health professional before use.

Keep out of reach of children.

Directions

Adults and children: (12 years and older) Chew 2 tablets every 2 - 3 hours or as symptoms occu, repeat hourly if needed. Do not exceed 19 tablets in 24 hours.

Children under 12 years: Ask a doctor

Other information

- calcium content per tablet: 168 mg

- Phenylketonurics: each tablet may contain 1.5 mg phenylalanine
- store at room temperature 59-86°F (15-30°C) in a dry place
- tamper-evident sealed packets
- do not use any opened or torn packets

Inactive ingredients

aspartame, croscarmellose sodium, magnesium stearate, maltodextrin, mint flavor, sorbitol

Questions or comments? Call 1-800-777-4908

PACKAGE LABEL

McKesson

Antacid Tablets

Calcium Carbonate 420 mg

NDC 68599-1411-3

Tablets for acid indigestion, gas, and heartburn.

2 Per Pack

250 Packs Per Box

MFR #87675